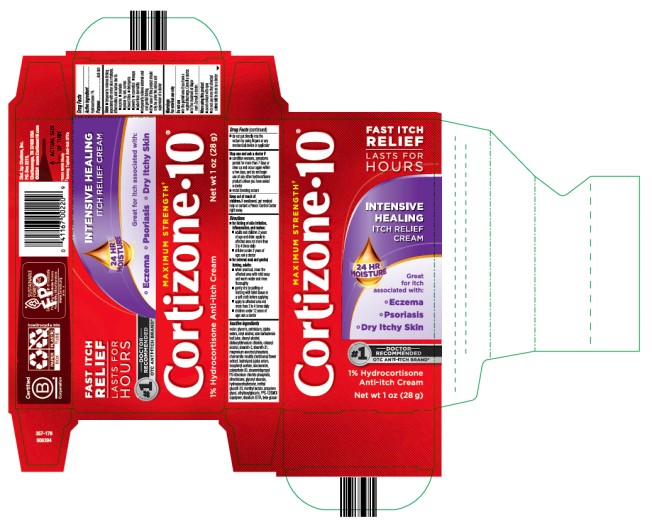 DRUG LABEL: Cortizone 10 Intensive Healing Itch Relief Cream
NDC: 41167-0023 | Form: CREAM
Manufacturer: Chattem, Inc.
Category: otc | Type: HUMAN OTC DRUG LABEL
Date: 20250201

ACTIVE INGREDIENTS: HYDROCORTISONE 1 g/100 g
INACTIVE INGREDIENTS: WATER; GLYCERIN; PETROLATUM; CETYL ALCOHOL; ALOE VERA LEAF; STEARYL ALCOHOL; DISTEARYLDIMONIUM CHLORIDE; CETEARYL ALCOHOL; STEARETH-2; STEARETH-21; MAGNESIUM ASCORBYL PHOSPHATE; CHAMOMILE; HYDROLYZED JOJOBA ESTERS; .ALPHA.-TOCOPHEROL ACETATE; NIACINAMIDE; POLYSORBATE 60; STEARAMIDOPROPYL PG-DIMONIUM CHLORIDE PHOSPHATE; DIMETHICONE; GLYCERYL STEARATE; HYDROXYACETOPHENONE; METHYL GLUCETH-20; MENTHYL LACTATE; PROPYLENE GLYCOL; ETHYLHEXYLGLYCERIN; PPG-12/SMDI COPOLYMER; DISODIUM EDTA-COPPER; JOJOBA OIL, RANDOMIZED

Cortizone-10 Intensive Healing Itch Relief Cream

Cortizone 10 Intensive Healing Itch Relief Cream

Drug Facts

Active ingredient

Hydrocortisone 1%

Purpose

Anti-itch

Uses

■ temporarily relieves itching associated with minor skin irritations, inflammation, and rashes due to:

■ eczema ■ psoriasis ■ poison ivy, oak, sumac ■ insect bites ■ detergents ■ jewelry

■ cosmetics ■ soaps ■ seborrheic dermatitis

■ temporarily relieves external anal and genital itching

■ other uses of this product should only be under the advice and supervision of a doctor

Warnings

For external use only

Do not use

■ in the genital area if you have a vaginal discharge. Consult a doctor. ■ for the treatment of diaper rash. Consult a doctor.

When using this product

■ avoid contact with eyes ■ do not use more than directed unless told to do so by a doctor ■ do not put directly into the rectum by using fingers or any mechanical device or applicator

Stop use and ask a doctor if

■ condition worsens, symptoms persist for more than 7 days or clear up and occur again within a few days, and do not begin use of any other hydrocortisone product unless you have asked a doctor

■ rectal bleeding occurs

Keep out of reach of children.

If swallowed, get medical help or contact a Poison Control Center right away.

Directions

■ for itching of skin irritation, inflammation, and rashes:

■ adults and children 2 years of age and older: apply to affected area not more than 3 to 4 times daily

■ children under 2 years of age: ask a doctor

■ for external anal and genital itching, adults:

■ when practical, clean the affected area with mild soap and warm water and rinse thoroughly

■ gently dry by patting or blotting with toilet tissue or a soft cloth before applying

■ apply to affected area not more than 3 to 4 times daily

■ children under 12 years of age: ask a doctor

Inactive ingredients

water, glycerin, petrolatum, jojoba esters, cetyl alcohol, aloe barbadensis leaf juice, stearyl alcohol, distearyldimonium chloride, cetearyl alcohol, steareth-2, steareth-21, magnesium ascorbyl phosphate, chamomilla recutita (matricaria) flower extract, hydrolyzed jojoba esters, tocopheryl acetate, niacinamide, polysorbate 60, stearamidopropyl PG-dimonium chloride phosphate, dimethicone, glyceryl stearate, hydroxyacetophenone, methyl gluceth-20, menthyl lactate, propylene glycol, ethylhexylglycerin, PPG-12/SMDI copolymer, disodium EDTA, beta-glucan

PRINCIPAL DISPLAY PANEL

Cortizone 10
Intensive Healing
Itch Relief
Cream
Net wt 1 oz (28 g)